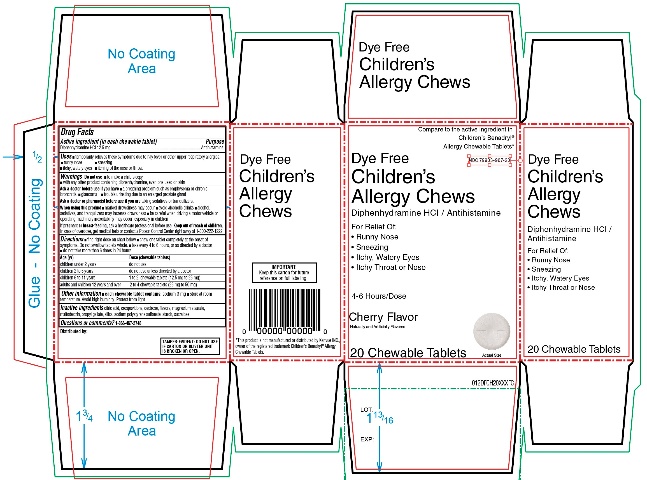 DRUG LABEL: Walmart
NDC: 79903-967 | Form: TABLET, CHEWABLE
Manufacturer: WALMART STORES INC
Category: otc | Type: HUMAN OTC DRUG LABEL
Date: 20260219

ACTIVE INGREDIENTS: DIPHENHYDRAMINE HYDROCHLORIDE 12.5 mg/1 1
INACTIVE INGREDIENTS: CITRIC ACID MONOHYDRATE; CROSPOVIDONE (120 .MU.M); DEXTROSE, UNSPECIFIED FORM; MAGNESIUM STEARATE; MALTODEXTRIN; PROPYL GALLATE; SILICON DIOXIDE; SODIUM POLYSTYRENE SULFONATE; STARCH, CORN; SUCRALOSE

Walmart Dye Free Children’s Allergy Chews Drug Facts

Active ingredient (in each chewable tablet)

Diphenhydramine HCl 12.5 mg

Purpose

Antihistamine

Uses

- temporarily relieves these symptoms due to hay fever or other upper respiratory allergies.
  - runny nose
  - itchy, watery eyes
  - sneezing
  - itching of the nose or throat

Warnings

Do not use

- to make a child sleepy
- with any other product containing diphenhydramine, even one used on skin

Ask a doctor before use if you have

- a breathing problem such as emphysema or chronic bronchitis
- glaucoma
- trouble urinating due to an enlarged prostate gland

Ask a doctor or pharmacist before use if you are

taking sedatives or tranquilizers.

When using this product

- marked drowsiness may occur
- avoid alcoholic drinks
- alcohol, sedatives, and tranquilizers may increase drowsiness
- be careful when driving a motor vehicle or operating machinery
- excitability may occur, especially in children

If pregnant or breast-feeding,

ask a health professional before use.

Keep out of reach of children.

In case of overdose, get medical help or contact a Poison Control Center right away at 1-800-222-1222.

Directions

- find right dose on chart below
- Chew one tablet completely at the onset of symptoms. Do not swallow tablets whole.
- take every 4 to 6 hours or as directed by a doctor
- do not take more than 6 times in 24 hours

Age (Yr) | Dose (Chewable tablets)
children under 2 years | do not use
children 2 to 5 years | do not use unless directed by a doctor
children 6 to 11 years | 1 to 2 chewable tablets (12.5 mg to 25 mg)
adults and children 12 years and over | 2 to 4 chewable tablets (25 mg to 50 mg)

Other information

- each chewable tablet contains: sodium 3 mg
- store at room temperature. Avoid high humidity. Protect from light

Inactive ingredients

Citric acid, crospovidone, dextrose, flavors, magnesium stearate, maltodextrin, propyl gallate, silica, sodium polystyrene sulfonate, starch, sucralose.

Questions or comments?

1-866-467-2748

Principal Display Panel

Compare to the active ingredient in Children's Benadryl® Allergy Chewable Tablets*

NDC 79903-967-20

Dye Free

Children’s Allergy Chews
Diphenhydramine HCl / Antihistamine

For Relief of:

- Runny Nose
- Sneezing
- Itchy Throat or Nose
- Itchy, Watery Eyes

4-6 Hours/Dose

Cherry Flavor

Naturally and Artificially Flavored

20 Chewable Tablets

TAMPER EVIDENT: DO NOT USE IF CARTON OR BLISTER UNIT IS BROKEN OR OPEN.

IMPORTANT: Keep this carton for future reference on full labeling.

*This product is not manufactured or distributed by Kenvue INC., owner of the registered trademark Children's Benadryl® Allergy Chewable Tablets.

Distributed by: